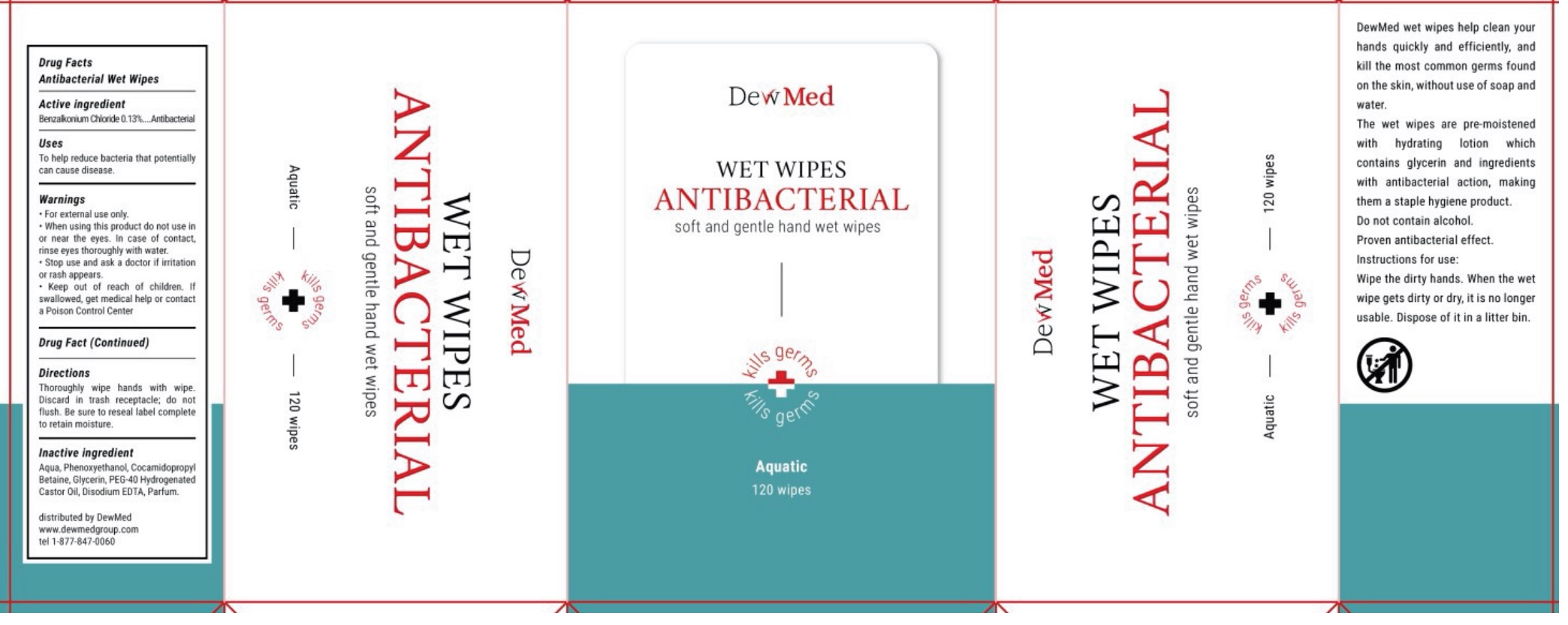 DRUG LABEL: DewMed Wet Wipes Antibacterial
NDC: 80065-003 | Form: CLOTH
Manufacturer: DewMed, LLC
Category: otc | Type: HUMAN OTC DRUG LABEL
Date: 20200928

ACTIVE INGREDIENTS: BENZALKONIUM CHLORIDE 1.3 mg/1 mL
INACTIVE INGREDIENTS: WATER; PHENOXYETHANOL; COCAMIDOPROPYL BETAINE; GLYCERIN; POLYOXYL 40 HYDROGENATED CASTOR OIL; EDETATE DISODIUM ANHYDROUS

DewMed Wet Wipes Antibacterial

Active ingredient

Benzalkonium Chloride 0.13%

PURPOSE

Antibacterial

Uses

To help reduce bacteria that potentially can cause disease.

Warnings

- For external use only.

When using this product

- do not use in or near the eyes. In case of contact, rinse eyes thoroughly with water.

Stop use and ask a doctor

if irritation or rash appears.

Keep out of reach of children.

If swallowed, get medical help or contact a Poison Control Center

Directions

Thoroughly wipe hands with wipe. Discard in trash receptacle; do not flush. Be sure to reseal label complete to retain moisture.

Inactive ingredients

Aqua, Phenoxyethanol, Cocamidopropyl Betaine, Glycerin, PEG-40 Hydrogenated Castor Oil, Disodium EDTA, Parfum.